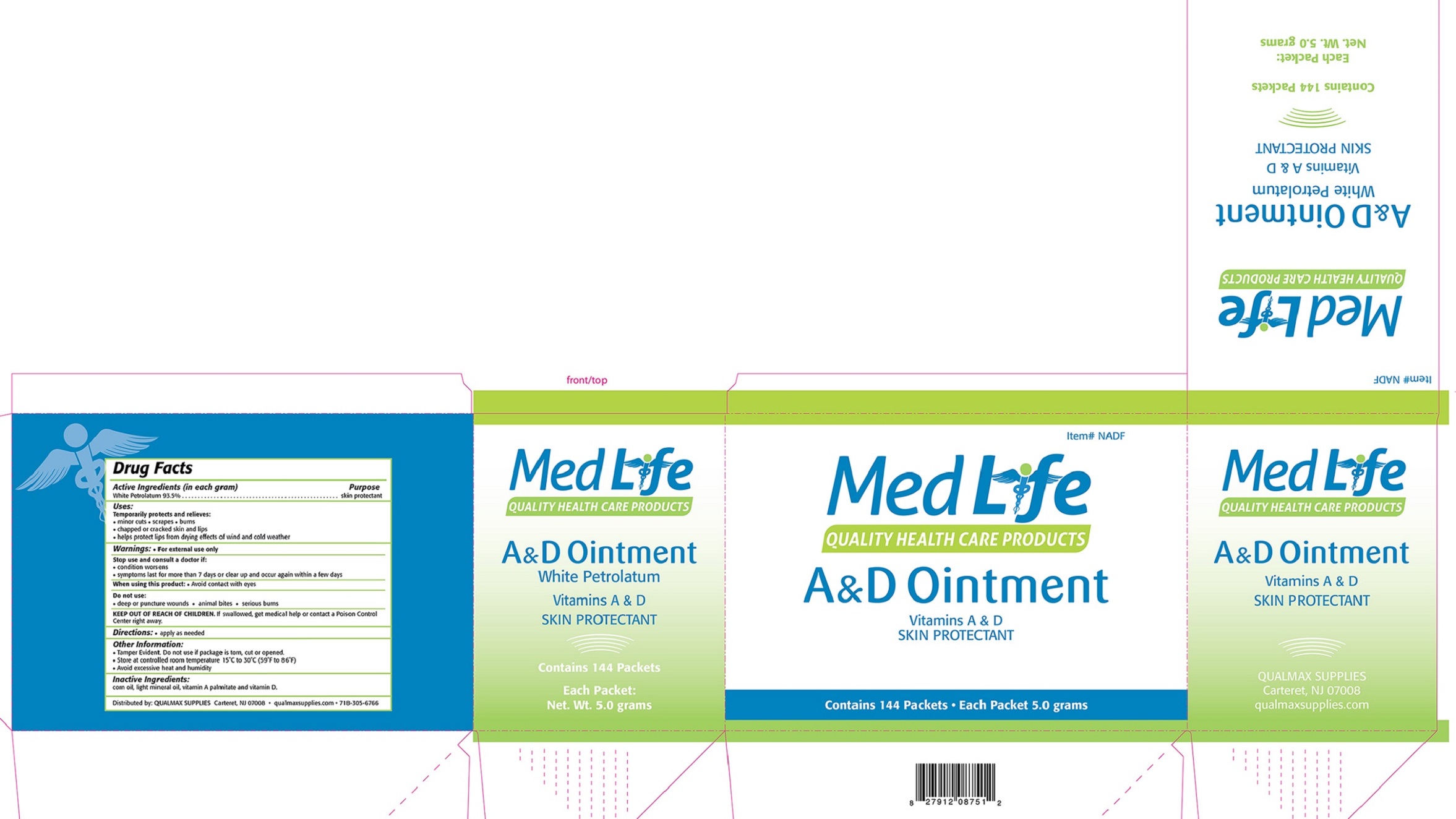 DRUG LABEL: MedLife A and D
NDC: 73285-375 | Form: OINTMENT
Manufacturer: Qualmax Supplies Inc.
Category: otc | Type: HUMAN OTC DRUG LABEL
Date: 20191105

ACTIVE INGREDIENTS: PETROLATUM 935 mg/1 g
INACTIVE INGREDIENTS: VITAMIN A; ERGOCALCIFEROL; CORN OIL; LIGHT MINERAL OIL

ACTIVE INGREDIENT

Active Ingredients (In Each Gram): White Petrolatum 93.5%

PURPOSE

skin protectant

Uses:

Temporarily protects and relieves:

• minor cuts • scrapes • burns

• chapped or cracked skin and lips

• helps protect lips from drying effects of wind and cold weather

Warnings:

• For external use only

Stop use and ask a doctor if:

• condition worsens

• symptoms last for more than 7 days or clear up and occur again within a few days

When using this product:

• avoid contact with eyes

Do not use:

• deep or puncture wounds

• animal bites

• serious burns

KEEP OUT OF REACH OF CHILDREN.

If swallowed, get medical help or contact a Poison Control Center right away.

Directions:

• apply as needed

Other Information:

• Tamper Evident. Do not use if packet is torn, cut or opened.

• Store at a controlled room temperature 15° to 30°C (59° to 86°F).

• Avoid excessive heat and humidity.

Inactive Ingredients:

corn oil, light mineral oil, vitamin A palmitate and vitamin D